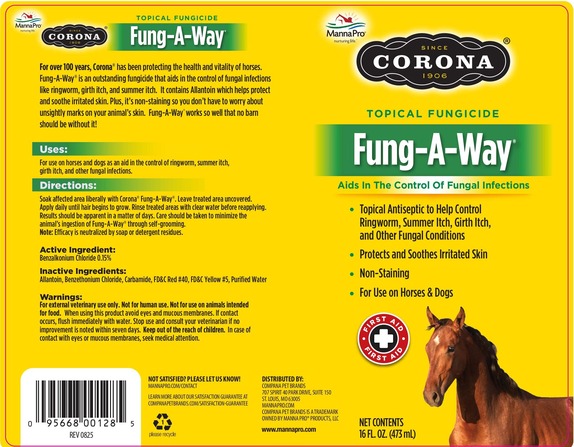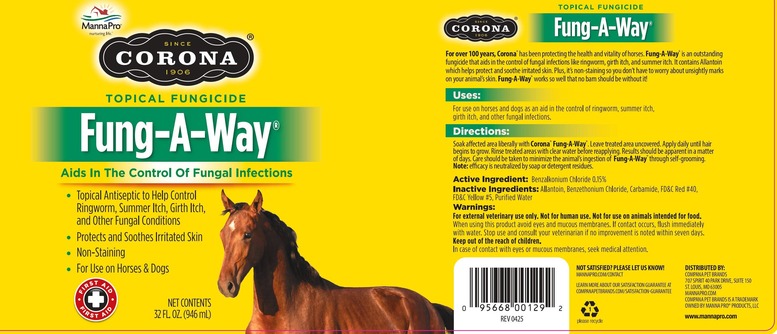 DRUG LABEL: HORSEMANS DREAM FUNG-A-WAY
NDC: 86077-1040 | Form: SOLUTION
Manufacturer: Manna Pro Products LLC
Category: animal | Type: OTC ANIMAL DRUG LABEL
Date: 20251211

ACTIVE INGREDIENTS: BENZALKONIUM CHLORIDE 0.15 g/100 mL

CORONA FUNG-A-WAY TOPICAL FUNGICIDE SOLUTION

Drug Facts

Active Ingredients: Benzalkonium chloride 0.15%

Purpose: Skin wound cleaner

Purpose: skin wound cleaner

Uses:

For use on horses and dogs as an aid in the control of ringworm, summer itch, girth itch, and other fungal infections.

Warnings

For external veterinary use only.

Not for human use.

Not for use on animals intended for food

When using this product avoid eyes and mucous membranes. If contact occurs, flush immediately with water.

Stop use and consult your veterinarian if no improvement is noted within seven days.

Keep out of reach of children. In case of contact with eyes or mucous membranes, seek medical attention.

Directions

Soak affected area liberally with topical fungicide solution. Leave treated area uncovered.

Apply daily until hair begins to grow.

Rinse treated areas with clear water before reapplying.

Results should be apparent in a matter of days. Care should be taken to minimize the animal's ingestion of topical fungicide solution through self-grooming.

Note: Efficacy is neutralized by soap or detergent residues.

Inactive Ingredients:

Allantoin, Benzethonium Chloride, Carbamide, FD&C Yellow #5, FD&C Red #40, Purified Water

PACKAGE LABEL

CORONA

SINCE 1906

TOPICAL FUNGICIDE

FUNG-A-WAY

Aids in The Control Of Fungal Infections

- Topical Antiseptic to Help Control Ringworm, Summer Itch, Girt Itch, and Other Fungal Conditions.

- Protects and Soothes Irritated Skin

- Non-Staining

- For Use on Horses & Dogs

Distributed By:

COMPANA PET BRANDS

707 Spirit 40 Park Drive

Suite 150

St. Louis, MO 63005

800-690-9908

COMPANA PET BRANDS IS A TRADEMARK

OWNED BY MANNA PRO PRODUCTS, LLC

www.mannapro.com